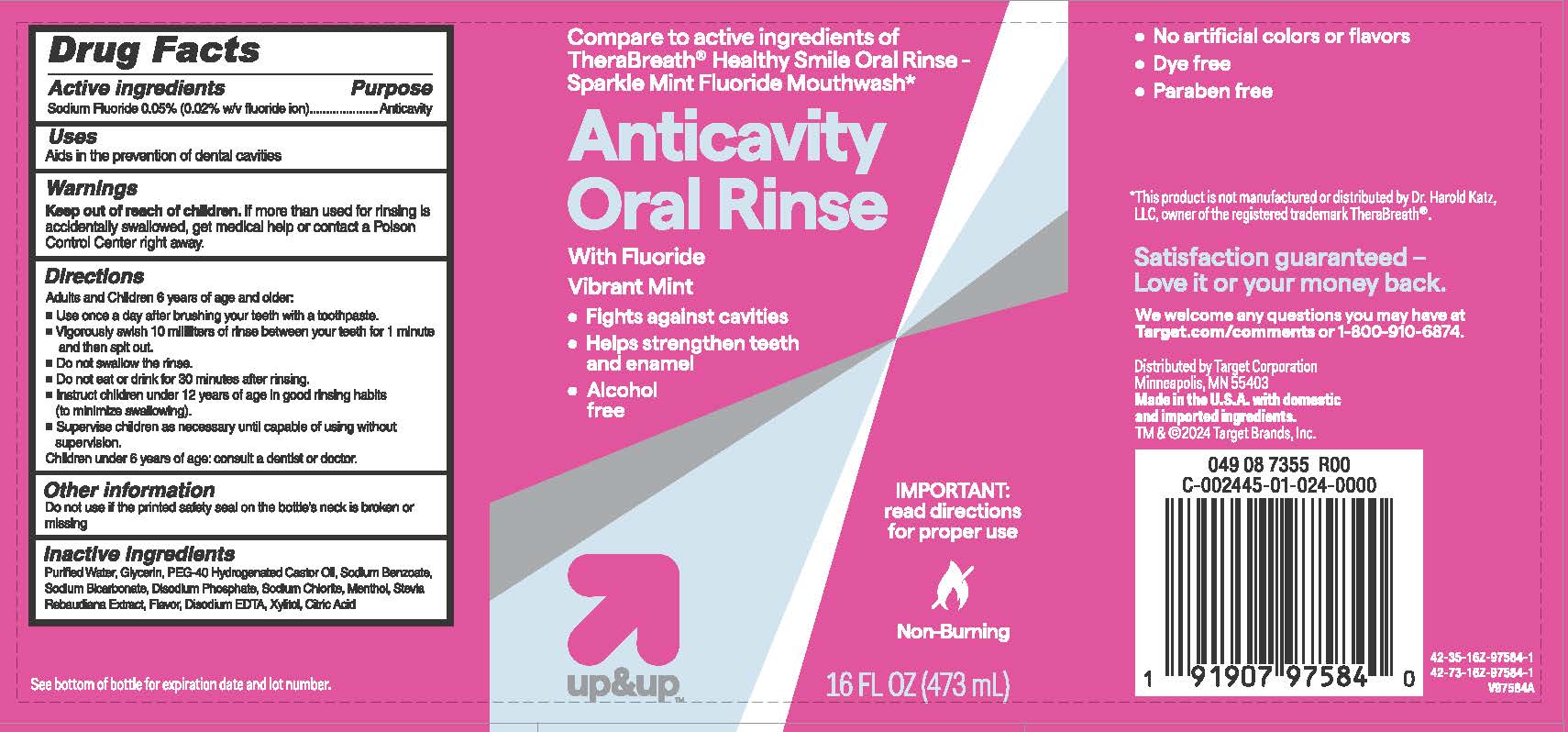 DRUG LABEL: TARGET UP AND UP ANTICAVITY
NDC: 82442-106 | Form: MOUTHWASH
Manufacturer: TARGET CORPORATION
Category: otc | Type: HUMAN OTC DRUG LABEL
Date: 20251008

ACTIVE INGREDIENTS: SODIUM FLUORIDE 0.05 g/100 mL
INACTIVE INGREDIENTS: CALCIUM DISODIUM EDTA; XYLITOL; CITRIC ACID; PEG-40 HYDROGENATED CASTOR OIL; SODIUM BICARBONATE; SODIUM CHLORITE; SODIUM BENZOATE; STEVIA REBAUDIUNA LEAF; MENTHOL; WATER; GLYCERIN; DISODIUM PHOSPHATE

TARGET UP & UP ANTICAVITY ORAL RINSE

Active ingredient

Sodium Fluoride....... 0.05%

Purpose

Anticavity

Uses

Aids in the prevention of dental cavities

Warnings

Keep out of reach of children.

If more than used for brushing is accidentally swallowed, get medical help or contact a Poison Control Center right away.

Directions

- Adults and Children 6 years of age and older:Use once a day after brushing your teeth with a toothpaste.
- Vigorously swish 10 milliliters of rinse between your teeth for 1 minute and then spit out.
- Do not swallow the rinse.
- Do not eat or drink for 30 minutes after rinsing.
- Instruct children under 12 years of age in good rinsing habits (to minimize swallowing).
- Supervise children as necessary until capable of using without supervision.
- Children under 6 years of age: consult a dentist or doctor.

Other information

Do not use if the printed safety seal on the bottle's neck is broken or missing.

Inactive ingredients

Water, Glycerin, PEG-40 Hydrogenated Castor Oil, Sodium Benzoate, Sodium Bicarbonate, Disodium Phosphate, Sodium Chlorite, Menthol, Stevia Rebaudiana Extract, Flavor, Disodium EDTA, Xylitol, Citric Acid